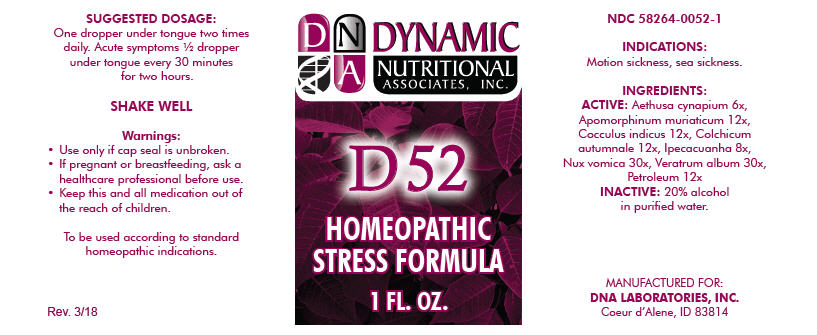 DRUG LABEL: D-52
NDC: 58264-0052 | Form: SOLUTION
Manufacturer: DNA Labs, Inc.
Category: homeopathic | Type: HUMAN OTC DRUG LABEL
Date: 20250113

ACTIVE INGREDIENTS: COLCHICUM AUTUMNALE BULB 12 [hp_X]/1 mL; IPECAC 8 [hp_X]/1 mL; STRYCHNOS NUX-VOMICA SEED 30 [hp_X]/1 mL; VERATRUM ALBUM ROOT 30 [hp_X]/1 mL; KEROSENE 12 [hp_X]/1 mL; AETHUSA CYNAPIUM 6 [hp_X]/1 mL; APOMORPHINE HYDROCHLORIDE 12 [hp_X]/1 mL; ANAMIRTA COCCULUS SEED 12 [hp_X]/1 mL
INACTIVE INGREDIENTS: ALCOHOL; WATER

D-52

NDC 58264-0052-1

INDICATIONS

PURPOSE

Motion sickness, sea sickness.

INGREDIENTS

ACTIVE

Aethusa cynapium 6x, Apomorphinum muriaticum 12x, Cocculus indicus 12x, Colchicum autumnale 12x, Ipecacuanha 8x, Nux vomica 30x, Veratrum album 30x, Petroleum 12x

INACTIVE

20% alcohol in purified water.

SUGGESTED DOSAGE

One dropper under tongue two times daily. Acute symptoms ½ dropper under tongue every 30 minutes for two hours.

STORAGE AND HANDLING

SHAKE WELL

Warnings

- Use only if cap seal is unbroken.

PREGNANCY OR BREAST FEEDING

- If pregnant or breastfeeding, ask a healthcare professional before use.

KEEP OUT OF REACH OF CHILDREN

- Keep this and all medication out of the reach of children.

To be used according to standard homeopathic indications.

PRINCIPAL DISPLAY PANEL - 1 FL. OZ. Bottle Label

DYNAMIC
NUTRITIONAL
ASSOCIATES, INC.

D 52

HOMEOPATHIC
STRESS FORMULA

1 FL. OZ.